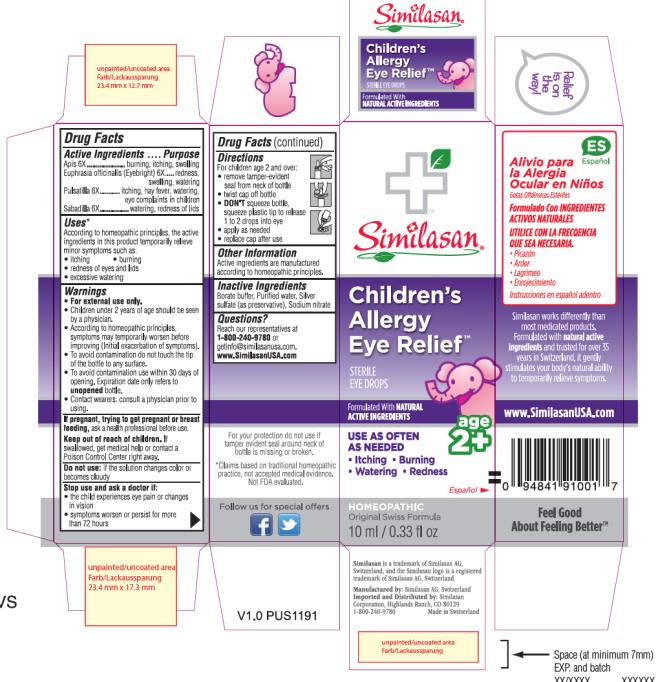 DRUG LABEL: Childrens Allergy Eye Relief
NDC: 53799-370 | Form: SOLUTION/ DROPS
Manufacturer: Similasan AG
Category: homeopathic | Type: HUMAN OTC DRUG LABEL
Date: 20201007

ACTIVE INGREDIENTS: APIS MELLIFERA 6 [hp_X]/10 mL; EUPHRASIA STRICTA 6 [hp_X]/10 mL; PULSATILLA PATENS WHOLE 6 [hp_X]/10 mL; SCHOENOCAULON OFFICINALE SEED 6 [hp_X]/10 mL
INACTIVE INGREDIENTS: WATER; SILVER SULFATE; SODIUM NITRATE

Childrens Allergy Eye Relief

Drug Facts – Children’s Allergy Eye Relief

Active Ingredients

Apis 6X

Euphrasia officinalis (Eyebright) 6X

Pulsatilla 6X

Sabadilla 6X

Purpose

burning, itching, swelling

redness, swelling, watering

itching, hay fever, watering, eye complaints in children

watering, redness of lids

Uses*

According to homeopathic principles, the active ingredients in this product temporarily relieve minor symptoms such as:

• itching

• burning

• redness of eyes and lids

• excessive watering

Warnings

• For external use only.

• Children under 2 years of age should be seen by a physician.

• According to homeopathic principles, symptoms may temporarily worsen before improving (Initial exacerbation of symptoms).

• To avoid contamination do not touch the tip of the bottle to any surface.

• To avoid contamination use within 30 days of opening. Expiration date only refers to unopened bottle.

• Contact wearers: consult a physician prior to using.

If pregnant, trying to get pregnant or breast feeding,

ask a health professional before use.

Keep out of reach of children.

If swallowed, get medical help or contact a Poison Control Center right away.

Do not use:

if the solution changes color or becomes cloudy

Stop use and ask a doctor if:

• the child experiences eye pain or changes in vision

• symptoms worsen or persist for more than 72 hours

Directions

For children age 2 and over:

• remove tamper-evident seal from neck of bottle

• twist cap off bottle

• DON'T squeeze bottle, squeeze plastic tip to release 1 to 2 drops into eye

• apply as needed

• replace cap after use

Other Information

Active ingredients are manufactured according to homeopathic principles.

Inactive Ingredients

Borate buffer, Purified water, Silver sulfate (as preservative), Sodium nitrate

Questions?

Reach our representatives at 1-800-240-9780 or getinfo@similasanusa.com.

www.SimilasanUSA.com

PRINCIPAL DISPLAY PANEL

Similasan
Children’s
Allergy
Eye Relief
STERILE EYE DROPS
10 ml / 0.33 fl oz